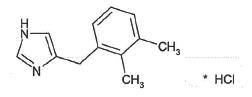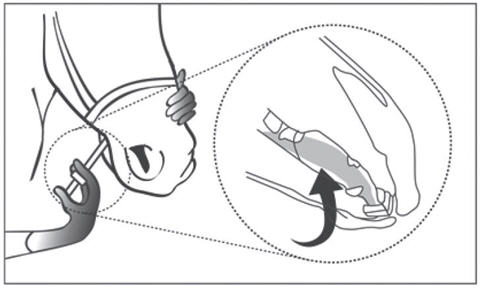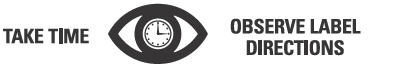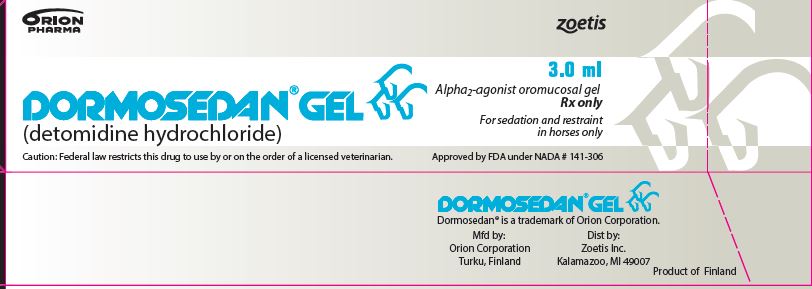 DRUG LABEL: Dormosedan
NDC: 54771-6291 | Form: GEL
Manufacturer: Zoetis Inc.
Category: animal | Type: PRESCRIPTION ANIMAL DRUG LABEL
Date: 20220516

ACTIVE INGREDIENTS: DETOMIDINE HYDROCHLORIDE 7.6 mg/1 mL

DORMOSEDAN® GEL

DORMOSEDAN® GEL
(detomidine hydrochloride)
Alpha2-agonist oromucosal gel

Rx only

For Sedation and Restraint in Horses Only

CAUTION

Federal law restricts this drug to use by or on the order of a licensed veterinarian.

DESCRIPTION

DORMOSEDAN (detomidine hydrochloride) GEL is a synthetic alpha2-adrenoreceptor agonist with sedative properties. Each mL of DORMOSEDAN GEL contains 7.6 mg detomidine hydrochloride. The chemical name is 1H imidazole, 4-[(2,3-dimethylphenyl) methyl]-hydrochloride. Detomidine hydrochloride is a white, crystalline, water-soluble substance having a molecular weight of 222.7. The molecular formula is C12H14N2•HCl and the structural formula is

INDICATIONS

DORMOSEDAN GEL is indicated for sedation and restraint in horses.

DOSAGE AND ADMINISTRATION

DORMOSEDAN GEL produces sedation when administered sublingually at 0.018 mg/lb (0.040 mg/kg). DORMOSEDAN GEL must be placed beneath the tongue of the horse and is not meant to be swallowed. The dosing syringe delivers the product in 0.25 mL increments. The following dosing table may be used to determine the correct dose of DORMOSEDAN GEL (Table 1).

Table 1: Sublingual dosing of DORMOSEDAN GEL
Approximate body weight (lb) | Range of doses (mg/lb) | Approximate body weight (kg) | Range of doses (mg/kg) | Dose volume (mL)
330 - 439 | 0.023 – 0.017 | 150 - 199 | 0.051 – 0.038 | 1.00
440 - 549 | 0.022 – 0.017 | 200 - 249 | 0.047 – 0-038 | 1.25
550 – 659 | 0.021 – 0.017 | 250 – 299 | 0.046 – 0.038 | 1.50
660 - 769 | 0.020 – 0.017 | 300 – 349 | 0.044 – 0.038 | 1.75
770 - 879 | 0.019 – 0.017 | 350 – 399 | 0.043 – 0.038 | 2.00
880 - 989 | 0.019 – 0.017 | 400 – 449 | 0.043 – 0.038 | 2.25
990 - 1099 | 0.019 – 0.017 | 450 – 499 | 0.042 – 0.038 | 2.50
1100 - 1209 | 0.019 – 0.017 | 500 – 549 | 0.042 – 0.038 | 2.75
1210 - 1320 | 0.019 – 0.017 | 550 - 600 | 0.041 – 0.038 | 3.00

Use impermeable gloves when handling the product. Remove the syringe from the outer carton. While holding the plunger, turn the ring-stop on the plunger until the ring is able to slide freely up and down the plunger. Position the ring in such a way that the side nearest the barrel is at the desired volume marking. Turn the ring to secure it in place. Make sure that the horse's mouth contains no feed. Remove the cap from the tip of the syringe and save for cap replacement. Insert the syringe tip into the horse's mouth from the side of the mouth, placing the syringe tip beneath the tongue at the level of the commisure of the mouth. Depress the plunger until the ring-stop contacts the barrel, depositing the product beneath the tongue.

The following picture demonstrates correct administration of DORMOSEDAN GEL beneath the tongue.

Take the syringe out of the horse's mouth, recap the syringe and return it to the outer carton for disposal. Remove gloves for disposal.

For the best results, allow adequate time (a minimum of 40 minutes) between administration of DORMOSEDAN GEL and beginning the procedure. In general, horses show sedative effects lasting approximately 90-180 minutes.

Withhold food and water until the sedative effects of the product wear off.

CONTRAINDICATIONS

DORMOSEDAN GEL is contraindicated in horses with known hypersensitivity to detomidine. Intravenous potentiated sulfonamides should not be used in anesthetized or sedated horses as potentially fatal dysrhythmias may occur.

Do not use DORMOSEDAN GEL in horses with pre-existing atrioventricular (AV) or sino-atrial (SA) blocks, respiratory disease, or chronic renal failure.

WARNINGS

For sublingual use in horses only. Do not use in horses intended for human consumption.

HUMAN WARNINGS

Not for human use. Keep out of the reach of children. Use impermeable gloves during drug administration and during procedures that require contact with the horse's mouth. Following sublingual administration of detomidine oromucosal gel, drug concentrations up to 0.072 mg/mL were measured at 30 minutes post dose in equine saliva, equivalent to less than one percent of the original detomidine concentration in the gel. Mean drug concentrations fall to less than 0.010 mg/mL by 2 hours after drug administration, after which a slow decline occurs for several additional hours.

DORMOSEDAN GEL can be absorbed following direct exposure to skin, eyes, or mouth, and may cause irritation. Skin and mucosal contact with the product should be avoided. Use impermeable gloves at all times.

In case of accidental eye exposure, rinse abundantly with fresh water. In case of accidental skin exposure, wash with soap and water. Remove contaminated clothing.

Appropriate precautions should be taken while handling and using gel syringes. Accidental exposure could cause adverse reactions, including sedation, hypotension, and bradycardia. Seek medical attention immediately but do not drive because sedation or changes in blood pressure may occur.

Individuals with cardiovascular disease (for example, hypertension or ischemic heart disease) should take special precautions to avoid exposure to this product.

Caution should be exercised when handling sedated horses. Handling or any other sudden stimuli, including noise, may cause a defense reaction in an animal that appears to be heavily sedated.

Rare cases of human abuse of detomidine products have been reported. DORMOSEDAN GEL should be managed to prevent the risk of diversion, through such measures as restriction of access and the use of drug accountability procedures appropriate to the clinical setting.

Note to physician: This product contains an alpha2-adrenoceptor agonist.

PRECAUTIONS

DORMOSEDAN GEL must be placed beneath the tongue of the horse. Unlike most oral veterinary products, this product is not meant to be swallowed. Swallowing could result in ineffectiveness.

DORMOSEDAN GEL does not provide analgesia. Do not use for painful procedures.

Do not use with other sedative drugs because the effects may be additive.

Repeat dosing has not been evaluated.

The use of an alpha2-agonist reversal agent with DORMOSEDAN GEL has not been evaluated.

Before initiating any procedure, allow sedation to fully develop. Nervous or excited horses with high levels of endogenous catecholamines may exhibit a reduced pharmacological response to alpha2-adrenoceptor agonists like detomidine. In agitated horses, the onset of sedative effects could be slowed, or the depth and duration of effects could be diminished or nonexistent. When the product is administered, the animal should be allowed to rest in a quiet place for a minimum of 40 minutes.

Do not use DORMOSEDAN GEL in horses with cardiovascular disease, respiratory disorders, liver or kidney diseases, or in conditions of shock, severe debilitation, or stress due to extreme heat, cold, fatigue, or high altitude. Protect treated horses from temperature extremes. As with all alpha2-adrenoceptor agonists, the potential for isolated cases of hypersensitivity, including paradoxical response (excitation), exists.

DORMOSEDAN GEL has not been evaluated in ponies, miniature horses, or horses younger than one year of age.

DORMOSEDAN GEL has not been evaluated for use in breeding, pregnant, or lactating horses.

ADVERSE REACTIONS

Clinical field study

In a US field study of 270 horses sedated to facilitate completion of various veterinary and husbandry procedures, the following adverse reactions were reported in 202 horses treated with DORMOSEDAN GEL and 68 horses treated with placebo:

Table 2: Adverse reactions (number of horses) during the clinical field study
Clinical Sign | DORMOSEDAN GEL N = 202 | Placebo N =68
Sweating | 20 | 0
Penile relaxation | 12 | 0
Bradycardia (≤ 20 bpm) | 11 | 0
Second degree AV block | 9 | 0
Frequent urination | 9 | 0
Piloerection | 4 | 0
Marked ataxia | 3 | 0
Facial/oral edema | 3 | 0
Hypersalivation | 2 | 0
Nasal discharge | 2 | 0
Flatulence | 1 | 0
Muscle tremors | 1 | 1
Epiphora | 1 | 0
Pale mucous membranes | 1 | 0
Swollen sheath | 1 | 0

In a laboratory study, transient erythema of the mucous membranes was seen in 2 (of 8) horses that received the recommended dose of detomidine gel.

Mild ataxia (horse stable but swaying slightly) was observed in 54% of DORMOSEDAN GEL-treated horses and in 4% of the placebotreated horses at 40 minutes post treatment administration. Moderate ataxia was observed in 25% of DORMOSEDAN GEL-treated horses (0% placebo) at 40 minutes post treatment. Moderate to marked ataxia continued to 90 minutes for 5% and to 120 minutes for 4% of DORMOSEDAN GEL-treated horses.

CONTACT INFORMATION

For a copy of the Safety Data Sheet or to report adverse reactions, call Zoetis Inc. at 1-888-963-8471. For additional information about adverse drug experience reporting for animal drugs, contact FDA at 1-888-FDA-VETS or www.fda.gov/reportanimalae.

CLINICAL PHARMACOLOGY

Detomidine is a potent non-narcotic alpha2-adrenoceptor agonist which produces sedation with a central effect inhibiting the transmission of noradrenalin-mediated nervous impulses. Blood pressure is initially increased due to peripheral vasoconstriction, subsequently dropping to normal or slightly below normal levels. Vasoconstriction may cause mucous membranes to appear pale or mildly cyanotic. This initial vasopressor response is accompanied by a compensatory marked decrease in heart rate mediated by a vagal baroreceptor. The peripheral pulse may feel weak and a transient change in the conductivity of the cardiac muscle may occur, as evidenced by first and second degree atrioventricular blocks. Other arrhythmias may occur. Detomidine also decreases the respiratory rate and decreases body temperature. Detomidine causes depression of gastrointestinal motility due to decrease in smooth muscle activity, increases blood glucose levels due to inhibition of insulin release, and increases production of urine 2 to 4 hours after treatment. In some horses, sweating, salivation and slight muscle tremors may be seen. Partial, transient penis prolapse may occur in stallions and geldings. Because of continued lowering of the head during sedation, mucus discharges from the nose with occasional swelling of the head, particularly around the eyes, may be seen.

Detomidine is oxidized mainly in the liver. Most metabolites are excreted in the urine. Halflife (T½) is 1-2 hours. Detomidine is rapidly distributed; volume of distribution (Vd) varies between 0.69 L/kg and 1.89 L/kg. Protein binding is about 85%.

Detomidine is a high extraction ratio drug. Alterations in liver blood flow (the site of detomidine metabolism) can change the rate of drug clearance and, consequently, drug exposure. The sedative effects of detomidine (using head droop as a marker for sedation) are highly correlated to blood concentration, regardless of the route of administration.

First pass effect results in a very small portion of drug reaching the systemic circulation if it is swallowed. Sedation achieved with the DORMOSEDAN GEL is attributable to sublingual drug absorption. Peak concentrations occur approximately 1.83 hours after sublingual administration of DORMOSEDAN GEL. The peak concentrations observed after administration of DORMOSEDAN GEL are approximately 40% of those observed after intramuscular injection of detomidine solution. The absolute bioavailability of detomidine in DORMOSEDAN GEL is 22%.

EFFECTIVENESS

A prospective, randomized, masked, multi-center study was conducted to evaluate under field conditions, whether DORMOSEDAN GEL provided sufficient sedation and restraint in horses to successfully conduct procedures requiring administration of a sedative. Two hundred and seventy client-owned horses of any breed or sex were sedated to facilitate grooming (including cleaning of the prepuce), hoof care, floating teeth (manually), passage of a nasogastric tube or endoscope, or radiography. Horses were enrolled in the study if they were a yearling or older, in satisfactory body condition, and had a history of requiring sedation or other means of strong restraint to enable similar procedures to be carried out. Horses were randomly assigned to receive DORMOSEDAN GEL sublingually at 0.040 mg/ kg or placebo gel. After administration of treatment, each horse's level of sedation, degree of ataxia, heart rate and rhythm, and respiratory rate were assessed and measured to recovery. After an appropriate period of time elapsed to allow sedation to develop, a study veterinarian assessed and scored the ability to attempt and to complete the veterinary or husbandry procedure.

One hundred and twenty-nine DORMOSEDAN GEL-treated and 42 placebo-treated horses were included in the statistical analysis of effectiveness. Ninety-nine horses were excluded from the analysis due to failure to meet inclusion criteria or due to major protocol deviations. The veterinary or husbandry procedure was successfully completed for 98 of 129 DORMOSEDAN GEL-treated horses (76%) but only 3 of 42 placebo-treated horses (7%) (Table 3). The difference between the two treatments was statistically significant (p=0.0005).

Table 3: Treatment success rates (number of horses) by treatment group
Ability to perform the procedure score [0: Poor – Strong resistance. 1: Fair. Moderate resistance. 2: Good. Some resistance, but the procedure could be performed. 3: Excellent. Procedure could be easily performed with insignificant resistance.] | DORMOSEDAN GEL N=129 | Placebo N=42
0 | 16 | 38
1 | 15 | 1
2 | 44 | 2
3 | 54 | 1
Success (score 2 or 3) | 98 | 3

* 0: Poor – Strong resistance. 1: Fair. Moderate resistance. 2: Good.Some resistance, but the procedure could be performed. 3: Excellent. Procedure could be easily performed with insignificant resistance

The following success rates with DORMOSEDAN GEL were recorded for electric clipping of hair (48%), cleaning the prepuce (81%), manual floating of teeth (89%), hoof trimming or shoeing (86%), passage of a nasogastric tube or endoscope (80%), or radiography (74%). At 40 minutes post dosing, 94% of DORMOSEDAN GEL-treated horses showed minimal, moderate or marked sedation compared with 14% of the horses treated with placebo. All DORMOSEDAN GEL-treated horses had recovered from sedation by 240 minutes post treatment.

DORMOSEDAN GEL was correctly administered sublingually (beneath the tongue) in 97% of horses with mild or no objection.

ANIMAL SAFETY

In a multiple dose target animal safety study, DORMOSEDAN GEL was administered on three consecutive days to 6 horses per treatment group at 0, 1, 3 and 5 times the recommended label dose of 0.040 mg/kg.

The recommended dose (1X) induced sedation. Head droop caused transient edema of the head area, nasal/ocular discharge, and congestion of oral mucous membranes. Ataxia, sweating, and reversible penile prolapse were observed. Erythematous mucous membranes were seen at the area of dose application in 2/6 horses. Transient reductions were seen in heart rate, respiratory rate, and gut motility. Electrocardiography revealed increased incidences of vagally mediated arrhythmias (sinus arrhythmia, sinus block, 1st and 2nd degree atrioventricular block) as well as atrial or ventricular premature beats in the majority of horses. No clinical abnormalities were associated with the transient arrhythmias. Excessive or erratic urination were seen in isolated cases.

Similar treatment related findings were seen in horses receiving 3X and 5X doses. In most cases the incidence, severity, and duration of the findings were dose dependent. All findings in all dose groups were representative of the alpha2-adrenoreceptor drugs used in horses.

STORAGE INFORMATION

Store at controlled room temperature 20-25°C (68-77°F), with excursions permitted to 15-30°C (59-86°F), in the original package.

HOW SUPPLIED

3.0 mL graduated oral dosing syringe, 7.6 mg/mL detomidine hydrochloride.

DORMOSEDAN® is a trademark of Orion Corporation.
Approved by FDA under NADA # 141-306

Mfd by:

Orion Corporation
Turku, Finland
Distributed by:
Zoetis Inc.
Kalamazoo, MI 49007
Revised: March 2022

CLIENT INFORMATION SHEET FOR OWNER/HANDLER USE AND SAFETY

This summary contains important information about Dormosedan (detomidine hydrochloride) Gel. You should read this information before you administer Dormosedan Gel to your horse. This sheet is provided only as a summary and does not take the place of instructions from your veterinarian. Talk to your veterinarian if you do not understand any of this information or if you want to know more about Dormosedan Gel.

What is Dormosedan Gel?

Dormosedan Gel is an oromucosal sedative containing detomidine hydrochloride. It is prescribed by veterinarians to allow procedures to be done in an anxious horse. Dormosedan Gel has not been shown to provide analgesia and should not be used for painful procedures.

How should the product be handled?

Always wear impermeable gloves when handling the dosing syringe with detomidine hydrochloride gel. Ask the veterinarian whether the gloves you plan to use are impermeable. For a minimum of 2 hours after administration, wear impermeable gloves when performing any tasks that require contact with the horse's mouth.

If you have or have had a history of cardiovascular disease (for example, hypertension or heart attack) take special precautions and avoid direct exposure to the dosing syringe. Do not come in contact with the mouth or any saliva of any horse that was treated with detomidine gel for a minimum of 2 hours.

What if I get the gel in my eyes or mouth?

Detomidine hydrochloride can be absorbed into your body after direct exposure through the eyes or mouth, and may cause irritation to these areas. In case of accidental eye exposure, flush with water for 15 minutes. If detomidine is exposed to the mucous membranes of the mouth, rinse without swallowing. In all cases of accidental exposure and possible ingestion, seek medical attention immediately. Accidental exposure could result in the drug affecting you, causing symptoms that include sleepiness, low blood pressure, and slower heart rate. DO NOT DRIVE because detomidine may cause you to feel drowsy or sleepy. Share the package information with your physician and tell the physician that the product contains an alpha2-adrenoceptor agonist.

What if I get the gel on my skin?
Detomidine hydrochloride can be absorbed into your body after direct exposure through the skin. In case of accidental skin exposure, wash with soap and water. Remove contaminated clothing. Contact your physician if you have any questions or concerns.
Contact Information
For a copy of the Safety Data Sheet or to report adverse reactions, call Zoetis Inc. at 1-888-963-8471. For additional information about adverse drug experience reporting for animal drugs, contact FDA at 1-888-FDA-VETS or www.fda.gov/reportanimalae.

How is Dormosedan Gel administered?

Dormosedan Gel should be given according to your veterinarian's instructions. Your veterinarian will tell you what amount of gel you should give to your horse. The appropriate dose is delivered beneath the tongue (sublingually) and is not meant to be swallowed. Make sure there is no food in the horse's mouth prior to administration.

The following drawing demonstrates correct administration of Dormosedan Gel beneath the tongue.

Following appropriate dosing of the gel, your horse should be kept in a quiet area until sedation is achieved.

If after 40 minutes there is inadequate sedation and you suspect that the horse swallowed or spit out some of the gel, contact your prescribing veterinarian. Do not repeat the dose.

If you believe the correct dose of detomidine gel was administered but the horse remains inadequately sedated, contact the prescribing veterinarian. Do not repeat the dose.

Contact your prescribing veterinarian immediately if the dosing syringe fails during the administration of detomidine gel and you are unsure if too much or too little of the dose was given.

Do not re-use partial dosing syringes. Any unused product or waste material should be disposed of in accordance with local requirements and Federal prescription drug disposal guidelines. Ask your veterinarian for this information.

What should I expect after administering Dormosedan Gel?

Following appropriate dosing of the gel, your horse should be kept in a quiet area. As the drug takes effect, you will typically see the head lower and the front legs plant in a firm stance. This will usually take about 40 minutes. You may also notice slight swaying, sweating, salivation and slight muscle tremors. Be careful when handling sedated horses. Handling or any other sudden stimuli, including noise, may cause a defense reaction (for example, kicking) even in a horse that appears to be fully sedated. It may take up to 3-4 hours for the horse to recover from sedation. Withhold food and water until the horse has recovered.

What else should I know about Dormosedan Gel?

As with all prescribed medicines, Dormosedan Gel should only be given to the horse for which it was prescribed. This sheet provides a summary of information about Dormosedan Gel. If you have any questions or concerns about Dormosedan Gel or its effects on your horse or yourself, talk to your veterinarian.
Revised: March 2022